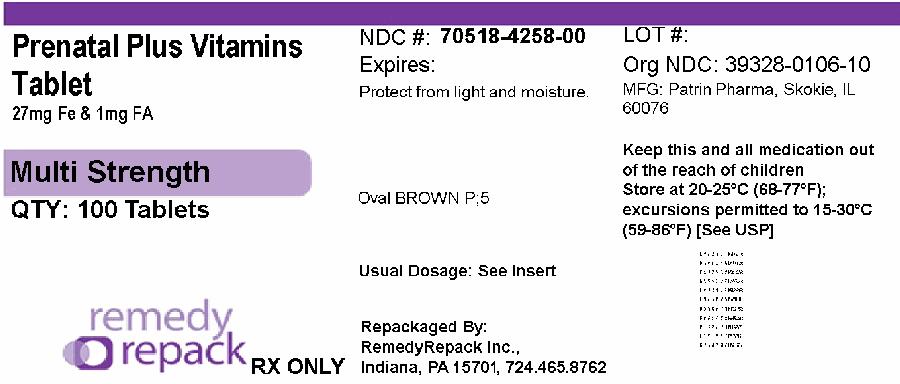 DRUG LABEL: Prenatal Plus Vitamins
NDC: 70518-4258 | Form: TABLET
Manufacturer: REMEDYREPACK INC.
Category: prescription | Type: HUMAN PRESCRIPTION DRUG LABEL
Date: 20250930

ACTIVE INGREDIENTS: VITAMIN A ACETATE 924 ug/1 1; BETA CAROTENE 276 ug/1 1; ASCORBIC ACID 120 mg/1 1; CHOLECALCIFEROL 10 ug/1 1; .ALPHA.-TOCOPHEROL ACETATE, DL- 10 mg/1 1; THIAMINE MONONITRATE 1.84 mg/1 1; RIBOFLAVIN 3 mg/1 1; NIACINAMIDE 20 mg/1 1; PYRIDOXINE HYDROCHLORIDE 10 mg/1 1; FOLIC ACID 1667 ug/1 1; CYANOCOBALAMIN 12 ug/1 1; CALCIUM CARBONATE 200 mg/1 1; FERROUS FUMARATE 27 mg/1 1; ZINC OXIDE 25 mg/1 1; CUPRIC OXIDE 2 mg/1 1
INACTIVE INGREDIENTS: HYPROMELLOSE, UNSPECIFIED; MAGNESIUM STEARATE; MALTODEXTRIN; MICROCRYSTALLINE CELLULOSE; POLYETHYLENE GLYCOL 400; STEARIC ACID; TITANIUM DIOXIDE; FD&C BLUE NO. 2; FD&C RED NO. 40; FD&C YELLOW NO. 6

Prenatal Vitamins Plus Low Iron

DESCRIPTION

Supplement Facts
Serving Size: 1 Tablet | Amount per Serving | % Daily Value [Daily Value is for Pregnant and Lactating Women]
Vitamin A | 1200 mcg | 92%
(Acetate and Beta Carotene) | RAE
Vitamin C (Ascorbic Acid) | 120 mg | 100%
Vitamin D-3 (Cholecalciferol) | 10 mcg | 67%
Vitamin E (dl-α Tocopheryl Acetate) | 10 mg | 53%
Vitamin B-1 (Thiamine Mononitrate) | 1.84 mg | 131%
Vitamin B-2 (Riboflavin) | 3 mg | 188%
Niacin (Niacinamide) | 20 mg | 111%
Vitamin B-6 (Pyridoxine HCl) | 10 mg | 500%
Folic Acid | 1667 mcg | 278%
 | DFE (1 mg)
Vitamin B-12 (Cyanocobalamin) | 12 mcg | 429%
Calcium (Calcium Carbonate) | 200 mg | 15%
Iron (Ferrous Fumarate) | 27 mg | 100%
Zinc (Zinc Oxide) | 25 mg | 192%
Copper(Cupric Oxide) | 2 mg | 154%

Other Ingredients:Hypromellose, Magnesium Stearate, Maltodextrin, Microcrystalline Cellulose, Polyethylene Glycol, Stearic Acid, Titanium Dioxide, FD&C Blue #2 lake, FD&C Red #40 lake, FD&C Yellow #6 lake

Description

Prenatal Plus Vitamins is a prescription folic acid containing dietary vitamin and mineral supplement for women before, during and after pregnancy.

Directions

Use before, during and after pregnancy under the supervision of a medical professional. One tablet daily or as prescribed.

Caution

Folic acid may partially correct the hematological damage due to Vitamin B-12 deficiency of pernicious anemia while the associated neurological damage progresses.

WARNING

Accidental overdose of iron-containing products is a leading cause of fatal poisoning in children under six. Keep this product out of the reach of children. In case of accidental overdose, call a Physician or Poison Control Center immediately.

Storage

Store at room temperature, USP. Protect from light and moisture.Dispense in a tight, light-resistant container. Contact with moisture may discolor or erode tablets.

Repackaged and Distributed By:

Remedy Repack, Inc.

625 Kolter Dr. Suite #4 Indiana, PA 1-724-465-8762

PACKAGE LABEL

DRUG: Prenatal Plus Vitamins

GENERIC: prenatal with ferrous fumarate and folic acid

DOSAGE: TABLET

ADMINSTRATION: ORAL

NDC: 70518-4258-0

COLOR: brown

SHAPE: OVAL

SCORE: No score

SIZE: 9 mm

IMPRINT: P;5

PACKAGING: 100 in 1 BOTTLE, PLASTIC

ACTIVE INGREDIENT(S):

- Vitamin A Acetate 924ug in 1
- Beta Carotene 276ug in 1
- Ascorbic Acid 120mg in 1
- Cholecalciferol 10ug in 1
- .Alpha.-TocopheroL Acetate, DL- 10mg in 1
- Thiamine Mononitrate 1.84mg in 1
- Riboflavin 3mg in 1
- Niacinamide 20mg in 1
- Pyridoxine Hydrochloride 10mg in 1
- Folic Acid 1667ug in 1
- Cyanocobalamin 12ug in 1
- Calcium Carbonate 200mg in 1
- Ferrous Fumarate 27mg in 1
- Zinc Oxide 25mg in 1
- Cupric Oxide 2mg in 1

INACTIVE INGREDIENT(S):

- Hypromellose, Unspecified
- Magnesium Stearate
- Maltodextrin
- Microcrystalline Cellulose
- Polyethylene Glycol 400
- Stearic Acid
- Titanium Dioxide
- FD&C Blue NO. 2
- FD&C Red NO. 40
- FD&C Yellow NO. 6